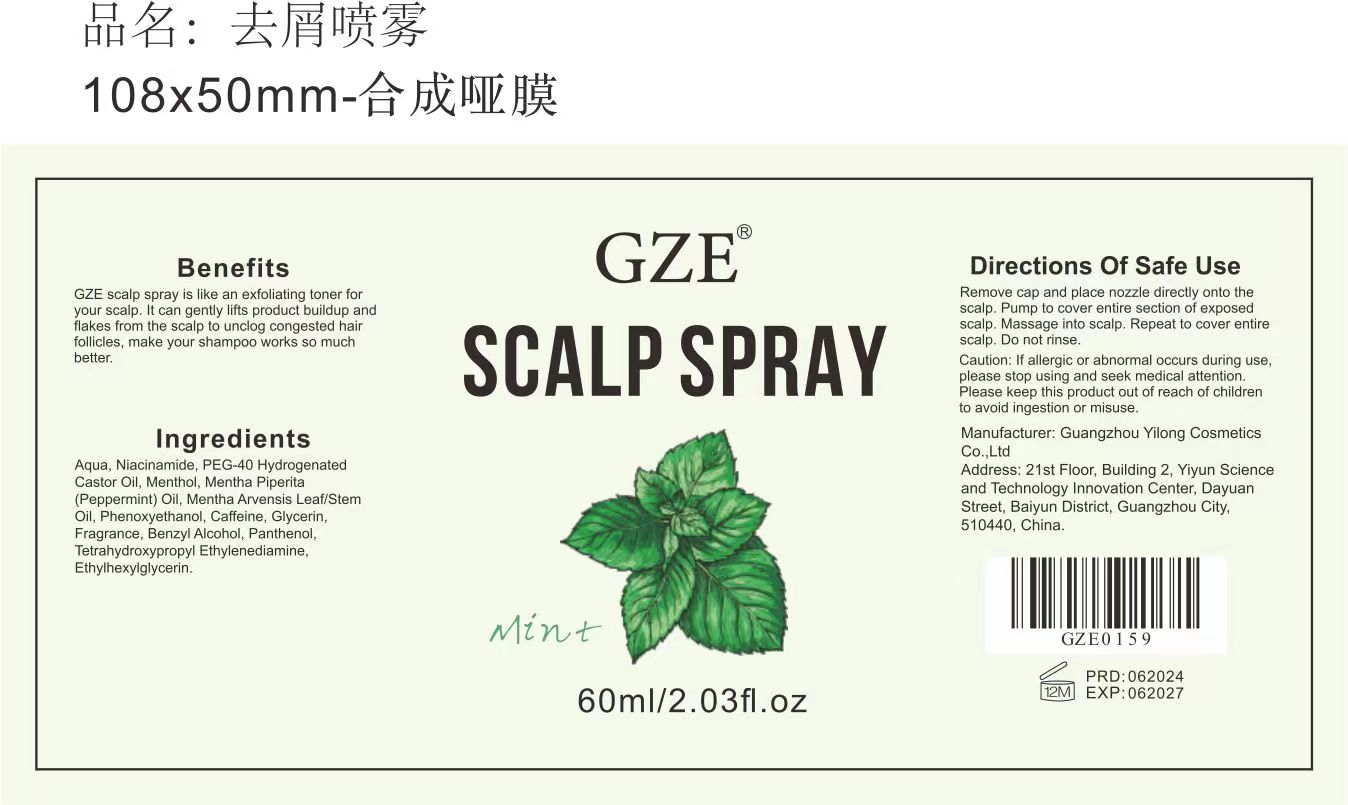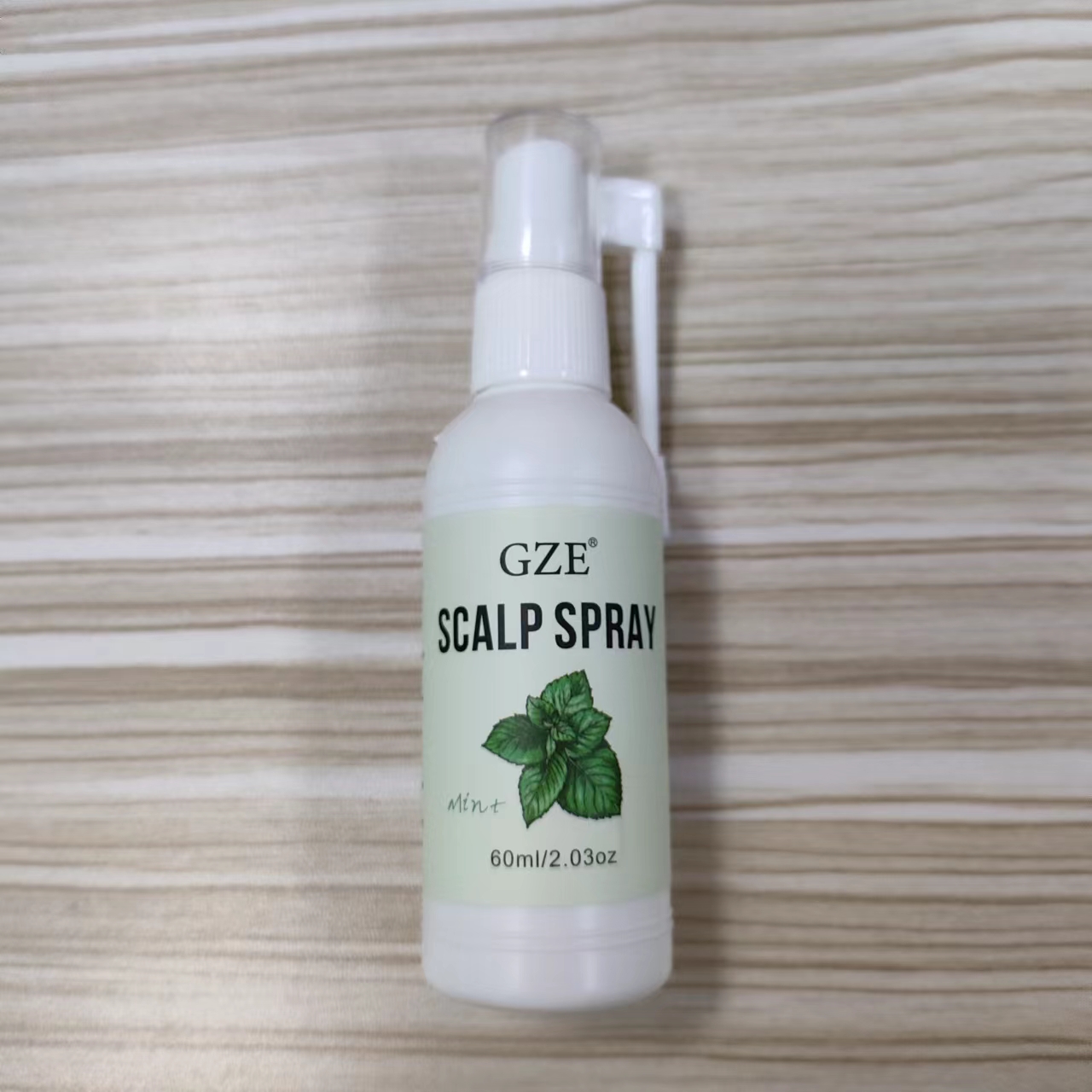 DRUG LABEL: GZE Scalp spary
NDC: 83566-159 | Form: SPRAY
Manufacturer: Guangzhou Yilong Cosmetics Co., Ltd
Category: otc | Type: HUMAN OTC DRUG LABEL
Date: 20240703

ACTIVE INGREDIENTS: MENTHOL 1 g/100 mL; CAFFEINE 2 g/100 mL
INACTIVE INGREDIENTS: WATER; PHENOXYETHANOL; MENTHA ARVENSIS LEAF OIL; GLYCERIN; PEPPERMINT OIL; NIACINAMIDE; POLYOXYL 40 HYDROGENATED CASTOR OIL; FRAGRANCE 13576; ETHYLENEDIAMINE; BENZYL ALCOHOL; PANTHENOL; ETHYLHEXYLGLYCERIN

GZE Scalp spary

ACTIVE INGREDIENT

MENTHOL 1%
CAFFEINE 2%

INACTIVE INGREDIENT

WATER
PHENOXYETHANOL
MENTHAARVENSIS LEAF OIL
GLYCERIN
PEPPERMINT OIL
NIACINAMIDE
POLYOXYL 40 HYDROGENATED CASTOR OIL
FRAGRANCE 13576
ETHYLENEDIAMINE
BENZYL ALCOHOL
PANTHENOL
ETHYLHEXYLGLYCERIN

PURPOSE

Scalp Cleansing

INDICATIONS AND USAGE

Remove cap and place nozzle directly onto the scalp.Pump to cover entire section of exposed scalp.Massage into scalp, Repeat to cover entire scalp. Do not rinse.

WARNINGS

For external use only.

Stop use and ask a doctor if rash occurs.

Do not use on damaged or broken skin.

When using this product keep out of eyes. Rinse with water to remove.

Keep out of reach of children. If swallowed, get medical help or contact a Poison Control Center right away.

DOSAGE AND ADMINISTRATION

After cleansing your hair and blow drying it, ruffle your hair and spray the nozzle along the hairline twice a week.